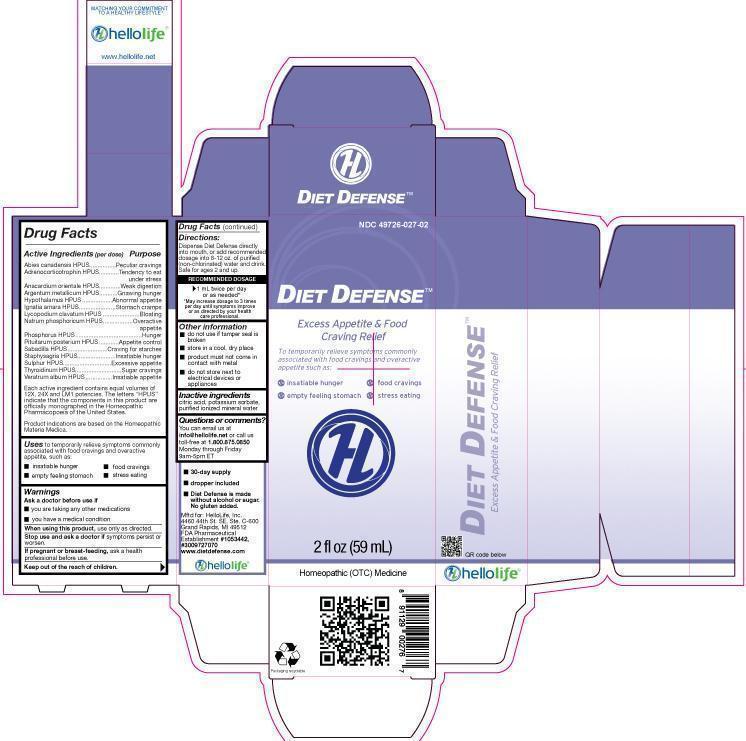 DRUG LABEL: Diet Defense
NDC: 49726-027 | Form: LIQUID
Manufacturer: Hello Life, Inc.
Category: homeopathic | Type: HUMAN OTC DRUG LABEL
Date: 20181226

ACTIVE INGREDIENTS: TSUGA CANADENSIS BARK 1 [hp_Q]/59 mL; SEMECARPUS ANACARDIUM JUICE 1 [hp_Q]/59 mL; SILVER 1 [hp_Q]/59 mL; CORTICOTROPIN 1 [hp_Q]/59 mL; BOS TAURUS HYPOTHALAMUS 1 [hp_Q]/59 mL; STRYCHNOS IGNATII SEED 1 [hp_Q]/59 mL; LYCOPODIUM CLAVATUM SPORE 1 [hp_Q]/59 mL; SODIUM PHOSPHATE, DIBASIC, HEPTAHYDRATE 1 [hp_Q]/59 mL; PHOSPHORUS 1 [hp_Q]/59 mL; SUS SCROFA PITUITARY GLAND 1 [hp_Q]/59 mL; SCHOENOCAULON OFFICINALE SEED 1 [hp_Q]/59 mL; DELPHINIUM STAPHISAGRIA SEED 1 [hp_Q]/59 mL; SULFUR 1 [hp_Q]/59 mL; THYROID, UNSPECIFIED 1 [hp_Q]/59 mL; VERATRUM ALBUM ROOT 1 [hp_Q]/59 mL
INACTIVE INGREDIENTS: WATER; CITRIC ACID MONOHYDRATE; POTASSIUM SORBATE

Drug Facts

Active Ingredients (per dose)

Abies canadensis HPUS

Adrenocorticotrophin HPUS

Anacardium orientale HPUS

Argentum metallicum HPUS

Hypothalamus HPUS

Ignatia amara HPUS

Lycopodium clavatum HPUS

Natrum phosphoricum HPUS

Phosphorus HPUS

Pituitarum posterium HPUS

Sabadilla HPUS

Staphysagria HPUS

Sulphur HPUS

Thyroidinum HPUS

Veratrum album HPUS

Each active ingredient contains equal volumes of 12X, 24X and LM1 potencies. The letters "HPUS" indicate that the components in this product are officially monographed in the Homeopathic Pharmacopoeia of the United States. Product indications are based on the Homeopathic Materia Medica.

Purpose

Abies canadensis HPUS.......................Peculiar cravings
Adrenocorticotrophin HPUS...................Tendency to eat under stress
Anacardium orientale HPUS..................Weak digestion
Argentum metallicum HPUS..................Gnawing hunger
Hypothalamus HPUS............................Abnormal appetite
Ignatia amara HPUS.............................Stomach cramps
Lycopodium clavatum HPUS.................Bloating
Natrum phosphoricum HPUS.................Overactive appetite
Phosphorus HPUS................................Hunger
Pituitarum posterium HPUS...................Appetite control
Sabadilla HPUS....................................Craving for starches
Staphysagria HPUS..............................Insatiable hunger
Sulphur HPUS......................................Excessive appetite
Thyroidinum HPUS...............................Sugar cravings
Veratrum album HPUS..........................Insatiable appetite

Uses

to temporarily relieve symptoms commonly associated with food cravings and overactive appetite, such as:

- insatiable hunger
- empty feeling stomach
- food cravings
- stress eating

Warnings

Ask a doctor before use if

- you are taking any other medications
- you have a medical condition

When using this product,

use only as directed.

Stop use and ask a doctor if

symptoms persist or worsen.

If pregnant or breast-feeding,

ask a health professional before use.

Keep out of the reach of children.

Directions:

Dispense Diet Defense directly into mouth, or add recommended dosage into 8-12 oz. of purified (non-chlorinated) water and drink. Safe for ages 2 and up.

RECOMMENDED DOSAGE
1 mL twice per day or as needed*
*May increase dosage to 3 times per day until symptoms improve or as directed by your health care professional.

Other information

-
  - do not use if tamper seal is broken
  - store in a cool, dry place
  - product must not come in contact with metal
  - do not store next to electrical devices or appliances.

Inactive ingredients

citric acid, potassium sorbate, purified ionized mineral water

Questions or comments?

You can email us at info@hellolife.net or call us toll-free at 1.800.875.0850 Monday through Friday 9am-5pm ET

DESCRIPTION

- 30-day supply
- Dropper included
- Diet Defense is made without alcohol or sugar. No gluten added.

Mftd for: HelloLife, Inc.
4460 44th St. SE, Ste. C-600
Grand Rapids, MI 49512
FDA Pharmaceutical Establishment
#1053442, #3009727070
www.dietdefense.com

Principal Display Panel

NDC 49726-027-02

DIET DEFENSETM

Excess Appetite and Food Craving Relief

To temporarily relieve symptoms commonly associated with food cravings and overactive appetite such as:

- insatiable hunger
- empty feeling stomach
- food cravings
- stress eating

2 fl oz (59 mL)
Homeopathic (OTC) Medicine